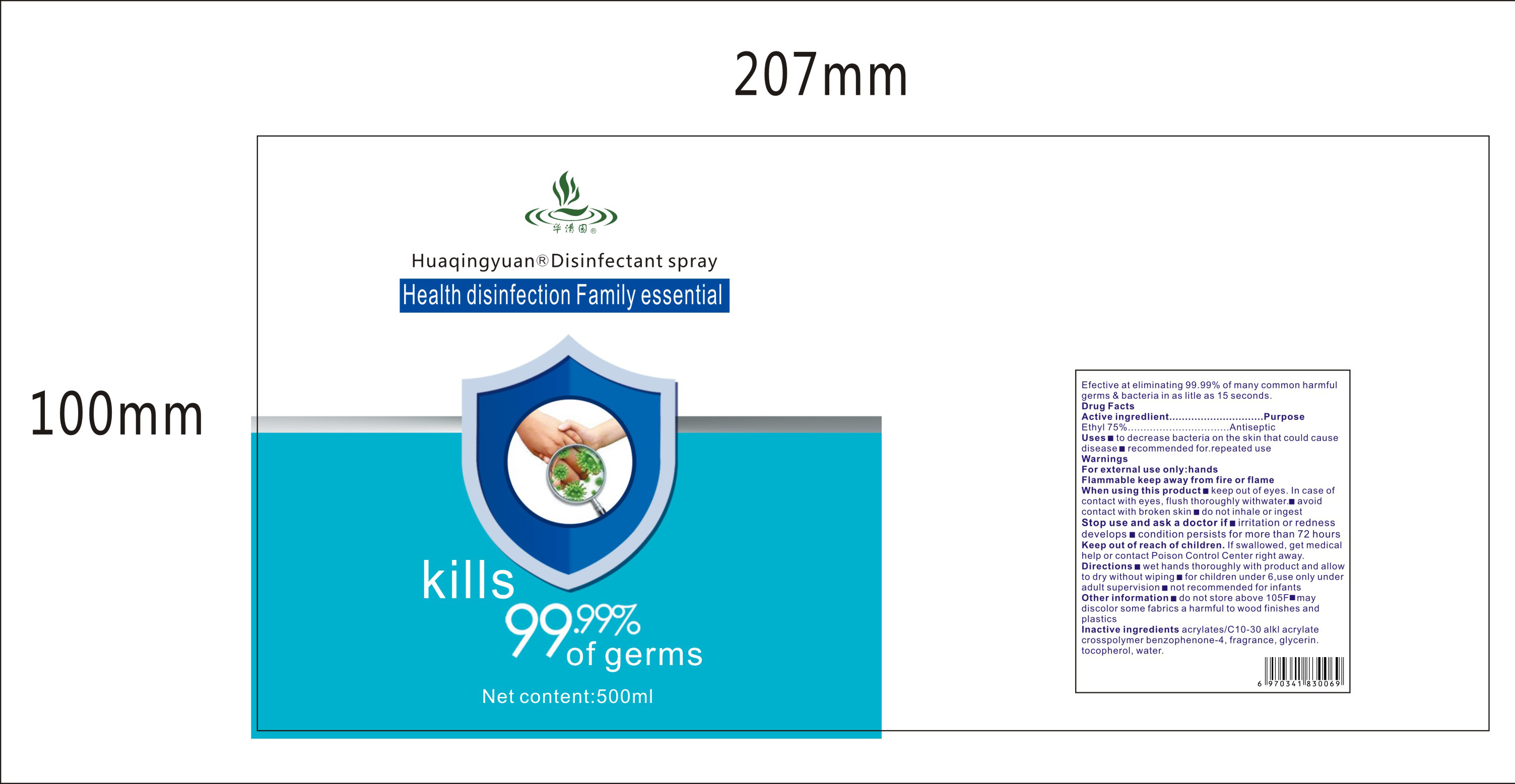 DRUG LABEL: Huaqingyuan Disinfectant
NDC: 54703-001 | Form: LIQUID
Manufacturer: Guangdong Huaqingyuan Biotechnology Co.,Ltd.
Category: otc | Type: HUMAN OTC DRUG LABEL
Date: 20200329

ACTIVE INGREDIENTS: HYPOCHLOROUS ACID 0.1 mg/500 mL
INACTIVE INGREDIENTS: SODIUM CHLORIDE; SODIUM PHOSPHATE, MONOBASIC; WATER

DOSAGE AND ADMINISTRATION

Do not store above 105°F.

May discolor some fabrics a harmful to wood finishes and plastics.

WARNINGS

For external use only: hands
Flammable keep away from fire or flame

ACTIVE INGREDIENT

Ethyl.

INDICATIONS AND USAGE

Wet hands thoroughly with product and allow to dry without wiping.

For children under 6,use only under adult supervision.

Not recommended for infants

PURPOSE

Disinfection
Sterilization
No Rinseing

INACTIVE INGREDIENT

Acrylates/C10-30 alkI acrylate crosspolymer benzophenone-4, fragrance, glycerin tocopherol, water.

keep out of reach of children